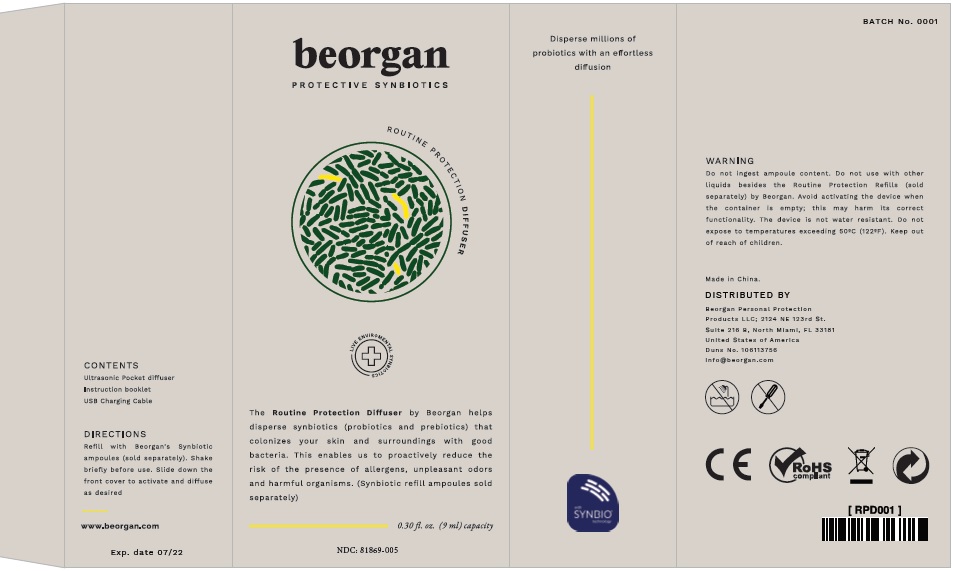 DRUG LABEL: Hand Sanitizer
NDC: 81869-005 | Form: SPRAY
Manufacturer: BEORGAN PERSONAL PROTECTION PRODUCTS LLC
Category: otc | Type: HUMAN OTC DRUG LABEL
Date: 20210513

ACTIVE INGREDIENTS: ISOPROPYL ALCOHOL 6.75 mL/9 mL
INACTIVE INGREDIENTS: WATER 0.1842 mL/9 mL; GLYCERIN 0.0145 mL/9 mL; HYDROGEN PEROXIDE 0.00125 mL/9 mL

Routine protection refill set ml 5 x 0.3 fl. oz. (9 ml)

Active Ingredient(s)

Alcohol 80% v/v. Purpose: Antiseptic

Purpose

Antiseptic, Hand Sanitizer

Use

to help reduce bacteria that potentially can cause disease. For use when soap and water are not available.

Warnings

For external use only. Flammable. Keep away from heat or flame

Do not use

in children less than 2 months of age
on open skin wounds

When using this product keep out of eyes, ears, and mouth. In case of contact with eyes, rinse eyes thoroughly with water.
Stop use and ask a doctor if irritation or rash occurs. These may be signs of a serious condition.
Keep out of reach of children. If swallowed, get medical help or contact a Poison Control Center right away.

Stop use and ask a doctor if irritation or rash occurs. These may be signs of a serious condition.

Keep out of reach of children. If swallowed, get medical help or contact a Poison Control Center right away.

DIRECTIONS

Place enough product on hands to cover all surfaces. Rub hands together until dry.
Supervise children under 6 years of age when using this product to avoid swallowing.

Other information

Store between 15-30C (59-86F)
Avoid freezing and excessive heat above 40C (104F)

Inactive ingredients

glycerin, hydrogen peroxide, purified water USP